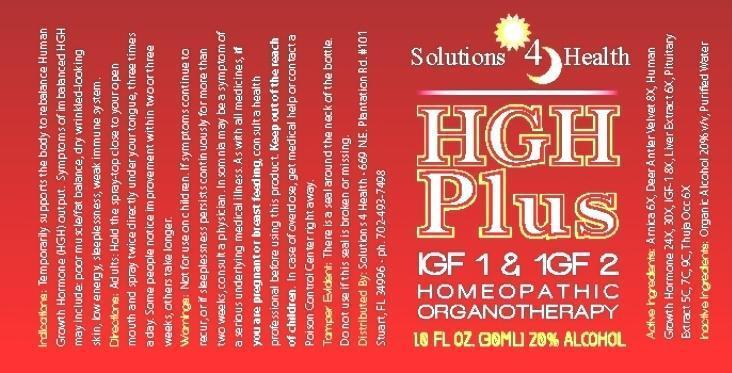 DRUG LABEL: HGH PLUS
NDC: 58095-0001 | Form: LIQUID
Manufacturer: Solutions 4 Health
Category: homeopathic | Type: HUMAN OTC DRUG LABEL
Date: 20131004

ACTIVE INGREDIENTS: ARNICA MONTANA 6 [hp_X]/1 mL; CERVUS NIPPON VELVET 8 [hp_X]/1 mL; BEEF LIVER 6 [hp_X]/1 mL; SOMATROPIN 24 [hp_X]/1 mL; MECASERMIN 8 [hp_X]/1 mL; BOS TAURUS PITUITARY GLAND 5 [hp_C]/1 mL; THUJA OCCIDENTALIS LEAF 6 [hp_X]/1 mL
INACTIVE INGREDIENTS: WATER; ALCOHOL

DRUG FACTS:

ACTIVE INGREDIENTS:

Arnica Montana 6X, Deer Antler Velvet 8X, Hepar Bovine 6X, HGH 24X, 30X, IGF-1 8X, Pituitaria Glandula Bovine 5C, 7C, 9C, Thuja Occidentalis 6X.

INDICATIONS:

Temporarily supports the body to rebalance Human Growth Hormone (HGH) output. Symptoms of imbalance HGH may include: poor muscle/fat balance. dry wrinkled-looking skin, low energy, sleeplessness, weak immune system.

WARNINGS:

Not for use on children. If symptoms continue to recur, or if sleeplessness persists continuously for more than two weeks, consult a physician. Insomnia may be a symptom of a serious underlying medical illness. As with all medicines, if you are pregnant or breast feeding, consult a health professional before using this product. Keep out of reach of children. In case of overdose, get medical help or contact a Poison Control Center right away.

Tamper Evident: There is a seal around the neck of the bottle. Do not use if this seal is broken or missing.

Keep out of reach of children. In case of overdose, get medical help or contact a Poison Control Center right away.

DIRECTIONS:

Adults: Hold the spray-top close to your open mouth and spray twice directly under your tongue, three times a day. Some people notice improvement within two or three weeks, others take longer.

INDICATIONS:

Temporarily supports the body to rebalance Human Growth Hormone (HGH) output. Symptoms of imbalance HGH may include: poor muscle/fat balance. dry wrinkled-looking skin, low energy, sleeplessness, weak immune system.

INACTIVE INGREDIENTS:

Purified Water, Organic Ethanol 20%

QUESTIONS:

Distributed By: Solutions 4 Health - 669 N.E. Plantation Rd. #101

Stuart, FL 34996 - ph. 702-493-7498

PACKAGE DISPLAY LABEL:

Solutions 4 Health

HGH Plus

IGF 1 & IGF 2

HOMEOPATHIC

ORGANOTHERAPY

1.0 FL. OZ. (30 ML)